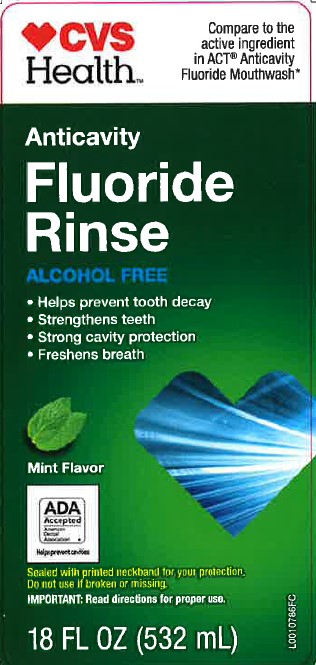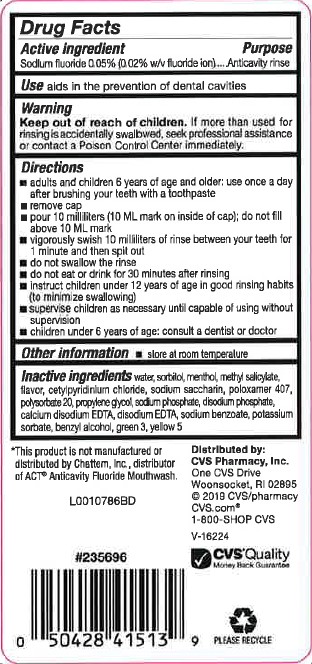 DRUG LABEL: Anticavity
NDC: 59779-213 | Form: RINSE
Manufacturer: CVS Pharmacy, Inc.
Category: otc | Type: HUMAN OTC DRUG LABEL
Date: 20260202

ACTIVE INGREDIENTS: SODIUM FLUORIDE 0.2 mg/1 mL
INACTIVE INGREDIENTS: WATER; SORBITOL; MENTHOL; METHYL SALICYLATE; CETYLPYRIDINIUM CHLORIDE; SACCHARIN SODIUM; POLOXAMER 407; POLYSORBATE 20; PROPYLENE GLYCOL; SODIUM PHOSPHATE, DIBASIC, ANHYDROUS; EDETATE CALCIUM DISODIUM ANHYDROUS; EDETATE DISODIUM ANHYDROUS; SODIUM BENZOATE; POTASSIUM SORBATE; BENZYL ALCOHOL; FD&C GREEN NO. 3; FD&C YELLOW NO. 5

CVS 213.002/213AE rev 2
Anticavity Fluoride Rinse, Mint

Active ingredient

Sodium Fluoride 0.05% (0.02% w/v fluoride ion)

Purpose

Anticavity rinse

Use

aids in the prevention of dental cavities

Warning

for this product

Keep out of reach of children

If more than used for rinsing is accidentally swallowed, seek professional assistance or contact a Poison Control Center immediately.

Directions

- adults and children 6 years of age and older: use once a day after brushing your teeth with toothpaste
- remove cap
- pour 10 milliliters (10 ML mark on the inside of cap); do not fill above 10 ML mark
- vigorously swish 10 millilters of rinse between your teeth for 1 minute and then spit out
- do not swallow the rinse
- do not eat or drink for 30 minutes after rinsing
- instruct children under 12 years of age in good rinsing habits (to minimize swallowing)
- supervise children as necessary until capable of using without supervision
- children under 6 years of age: consult a dentist or doctor

Other information

- store at room temperature

Inactive ingredients

water, sorbitol, menthol, methyl salicylate, flavor, cetylpyridinium chloride, sodium saccharin, poloxamer 407, polysorbate 20, propylene glycol, sodium phosphate, disodium phosphate, calcium disodium EDTA, disodium EDTA, sodium benzoate, potassium sorbate, benzyl alcohol, green 3, yellow 5

ADVERSE REACTION

*This product is not manufactured or distributed by Chattem, Inc., distributor of ACTAnticavity Fluoride Mouthwash.

Distributed by:

CVS Pharmacy, Inc

One CVS Drive

Woosocket, RI 02895

(c) 2019 CVS/pharmacy

CVS.com

1-800-SHOP CVS

CVS Quality

Money Back Guarantee

PLEASE RECYCLE

Principal display panel

CVS HEALTH™

Compare to the active ingredient in ACT®Anticavity Fluoride Mouthwash*

Anticavity

Fluoride

Rinse

ALCOHOL FREE

- Helps prevent tooth decay
- Strengthens teeth
- Strong cavity protection
- Freshens breath

Mint Flavor

ADA Accepted

American Dental Association

Helps prevent cavities

Sealed with printed neckband for your protection.

Do not use if broken or missing.

IMPORTANT: Read Directions for proper use.

18 FL OZ (532 mL)